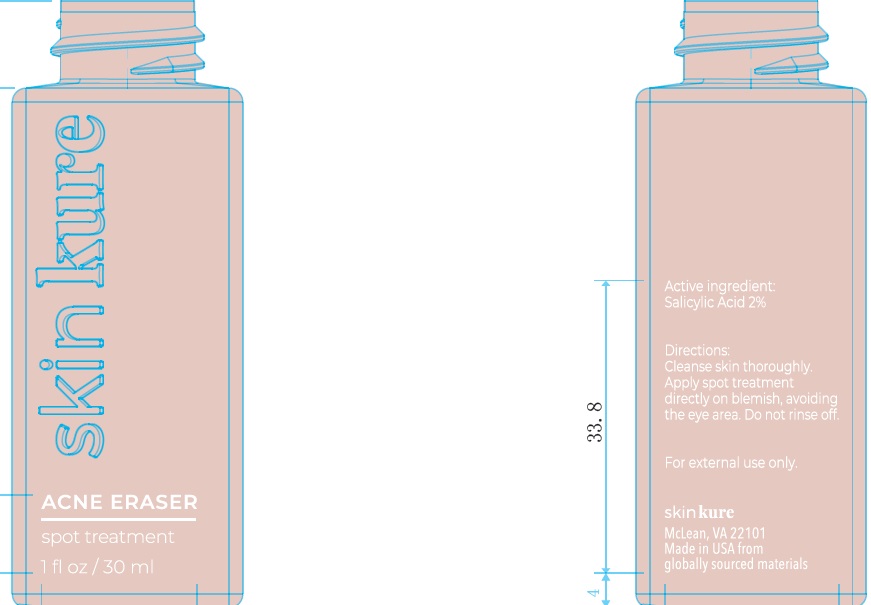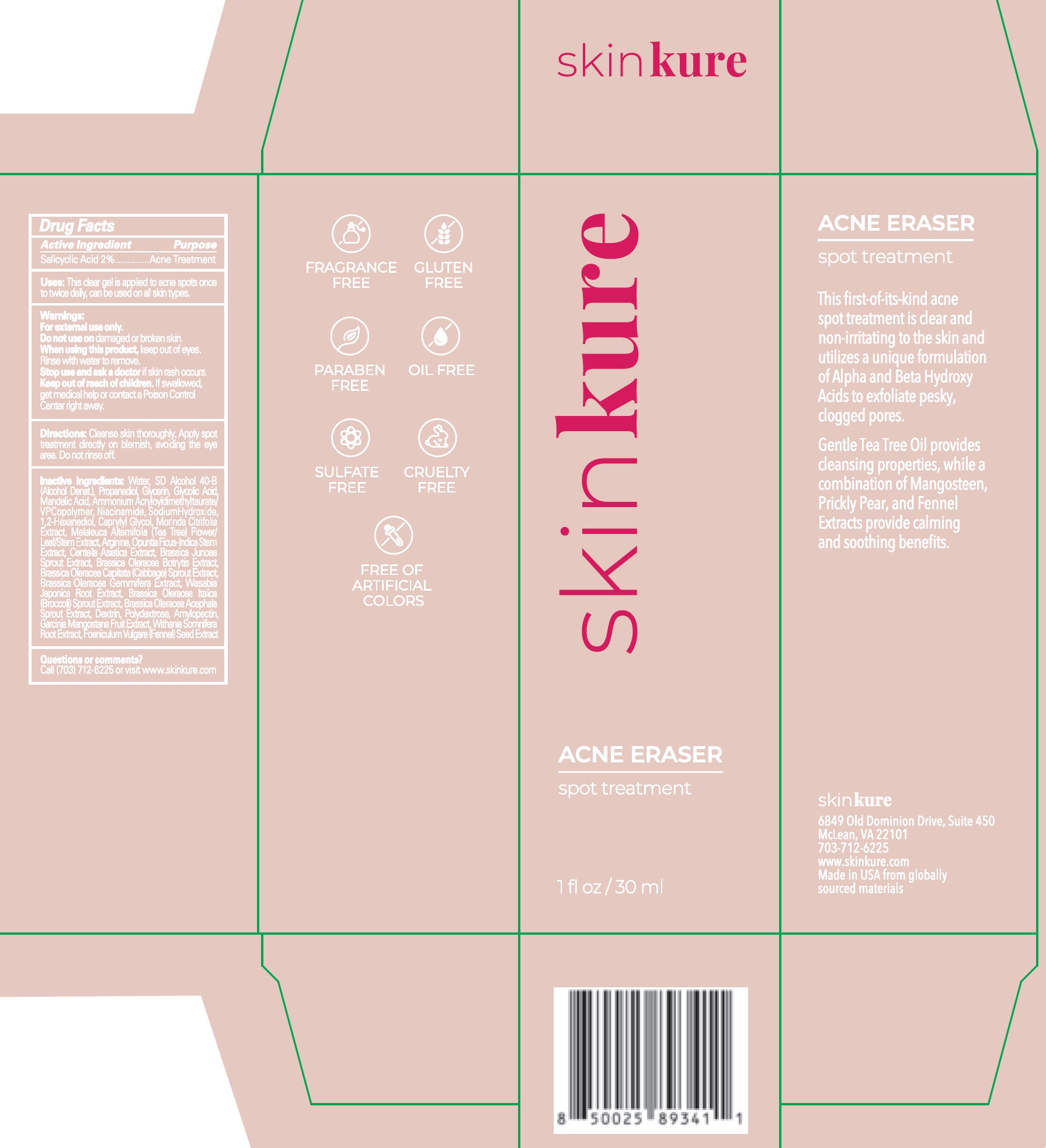 DRUG LABEL: Skinkure Acne Eraser Spot Treatment
NDC: 83865-100 | Form: GEL
Manufacturer: SKINKURE, LLC
Category: otc | Type: HUMAN OTC DRUG LABEL
Date: 20260123

ACTIVE INGREDIENTS: SALICYLIC ACID 20 mg/1 mL
INACTIVE INGREDIENTS: WATER; PROPANEDIOL; GLYCERIN; GLYCOLIC ACID; MANDELIC ACID; AMMONIUM ACRYLOYLDIMETHYLTAURATE/VP COPOLYMER; NIACINAMIDE; SODIUM HYDROXIDE; 1,2-HEXANEDIOL; CAPRYLYL GLYCOL; MORINDA CITRIFOLIA LEAF; MELALEUCA ALTERNIFOLIA FLOWERING TOP; ARGININE; OPUNTIA FICUS-INDICA STEM; CENTELLA ASIATICA TRITERPENOIDS; WASABI ROOT; BROCCOLI SPROUT; POLYDEXTROSE; GARCINIA MANGOSTANA FRUIT; WITHANIA SOMNIFERA ROOT; FENNEL SEED

Skinkure Acne Eraser Spot Treatment

Active Ingredient

Salicylic Acid 2%

Purpose

Acne Treatment

Uses:

This clear gel is applied to acne spots once to twice daily, can be used on all skin types.

Warnings:

For external use only.

Do not use on

damaged or broken skin.

When using this product,

keep out of eyes. Rinse with water to remove.

Stop use and ask a doctor

if skin rash occurs.

Keep out of reach of children.

If swallowed, get medical help or contact a Poison Control Center raight away.

Directions:

Cleanse skin thoroughly. Apply spot treatment directly on blemish, avoiding the eye area. Do not rinse off.

Inactive Ingredients:

Water, SD Alcohol 40-B (Alcohol Denat), Propanediol, Glycerin, Glycolic Acid, Mandelic Acid, Ammonium Acryloyldimethyltaurate/VPCopolymer, Niacinamide, SodiumHydroxide, 1,2-Hexanediol, Caprylyl Glycol, Morinda Citrifolia Extract, Melaleuca Alternifolia (Tea Tree) Flower/Leaf/Stem Extract, Arginine, Opuntia Ficus-Indica Stem Extract, Centella Asiatica Extract, Brassica Juncea Sprout Extract, Brassica Oleracea Botrytis Extract, Brassica Oleracea Capitata (Cabbage) Sprout Extract, Brassica Oleracea Gemmifera Extract, Wasabia Japonica Root Extract, Brassica Oleracea Italica (Broccoli) SproutExtract, Brassica Oleracea Acephala Sprout Extract, Dextrin, Polydextrose, Amylopectin, Garcinia Mangostana Fruit Extract, Withania Somnifera Root Extract, Foeniculum Vulgare (Fennel) Seed Extract

Questions or comments?

Call (703) 712-6225 or visit www.skinkure.com